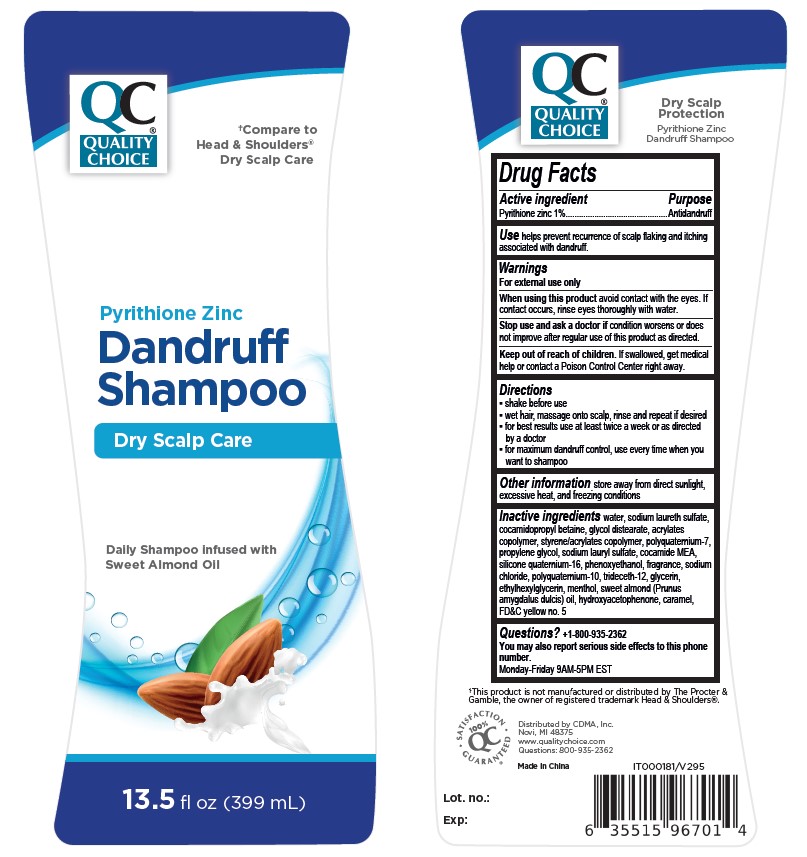 DRUG LABEL: Quality Choice Dandruff Dry Scalp Care
NDC: 83324-322 | Form: LOTION/SHAMPOO
Manufacturer: CHAIN DRUG MARKETING ASSOCIATION, INC.
Category: otc | Type: HUMAN OTC DRUG LABEL
Date: 20250124

ACTIVE INGREDIENTS: PYRITHIONE ZINC 10 mg/1 mL
INACTIVE INGREDIENTS: PHENOXYETHANOL; GLYCERIN; PRUNUS AMYGDALUS DULCIS (SWEET ALMOND) OIL; FD&C YELLOW NO. 5; POLYQUATERNIUM-10 (1000 MPA.S AT 2%); SODIUM CHLORIDE; BUTYL ACRYLATE/METHYL METHACRYLATE/METHACRYLIC ACID COPOLYMER (18000 MW); POLYQUATERNIUM-7; QUATERNIUM-16; COCAMIDOPROPYL BETAINE; TRIDECETH-12; ETHYLHEXYLGLYCERIN; MENTHOL; HYDROXYACETOPHENONE; GLYCOL DISTEARATE; SODIUM LAURYL SULFATE; COCAMIDE MEA; SODIUM LAURETH SULFATE; WATER; PROPYLENE GLYCOL; CARAMEL

Dandruff Dry Scalp Care Shampoo QC

Active Ingredient

Pyrithione zinc

Purpose

Antidandruff

Use

helps prevent recurrence of scalp flaking and itching associated with dandruff.

Warnings

For external use only

When using this product

avoid contact with the eyes. If contact occurs, rinse eyes thoroughly with water

Stop use and ask a doctor if

condition worsens or does not improve after regular use of this product as directed

Keep out of reach of children

If swallowed, get medical help or contact a Poison Control Center right away

Directions

- shake before use
- wet hair, massage onto scalp, rinse and repeat if desired
- for best results use at least twice a week or as directed by a doctor
- for maximum dandruff control, use every time when you want to shampoo

Other information

store away from direct sunlight, excessive heat, and freezing conditions

Inactive ingredients

water, sodium laureth sulfate, cocamidopropyl betaine, glycol distearate, acrylates copolymer, styrene/acrylates copolymer, polyquaternium-7, propylene glycol, sodium lauryl sulfate, cocamide MEA, silicone quaternium-16, phenoxyethanol, fragrance, sodium chloride, polyquaternium-10, trideceth-12, glycerin, ethylhexylglycerin, menthol, sweet almond (Prunus amygdalus dulcis) oil, hydroxyacetophenone, caramel, FD&C yellow no. 5

Questions?

+1-800-935-2362
You may also report serious side effects to this phone number.
Monday-Friday 9AM-5PM EST